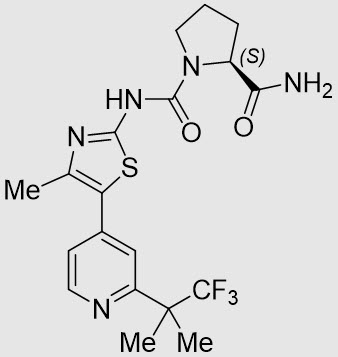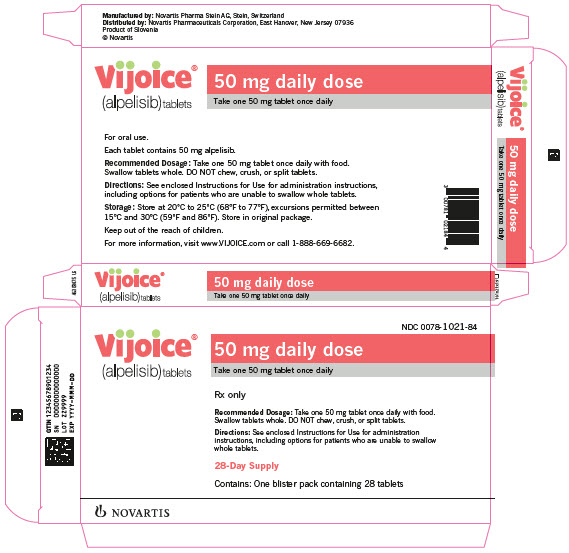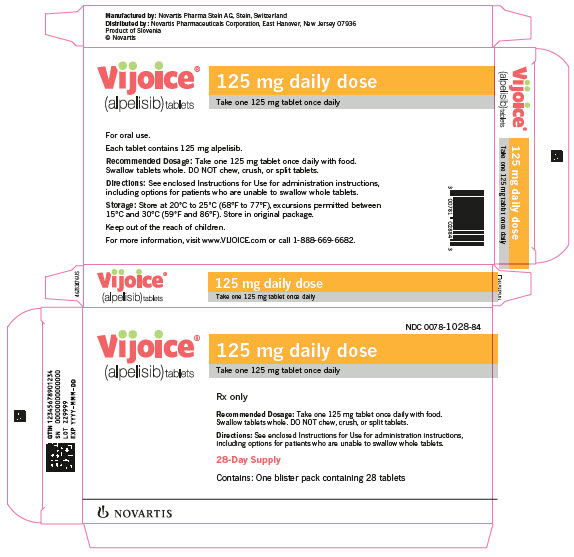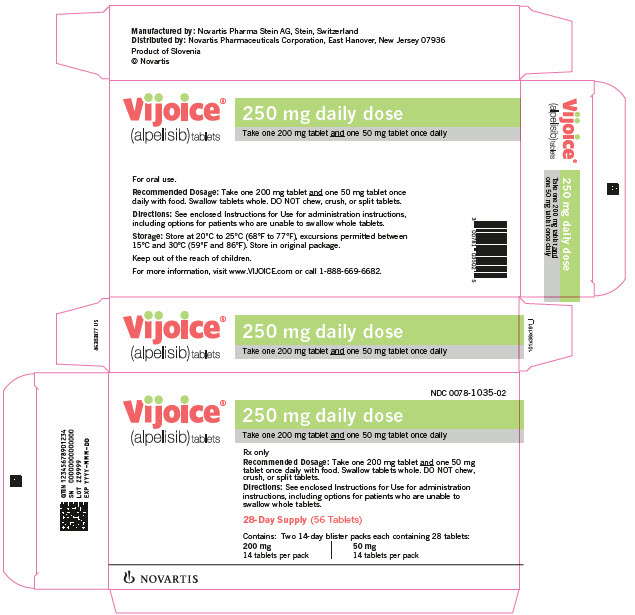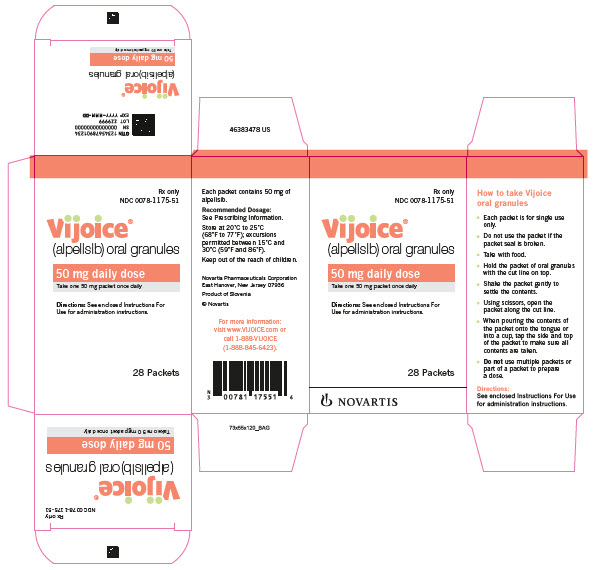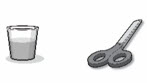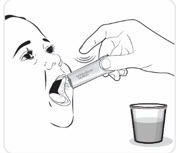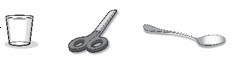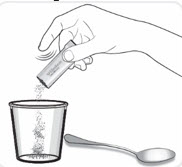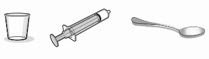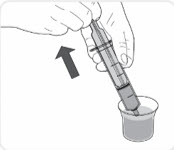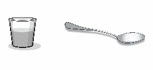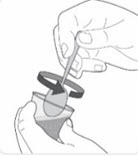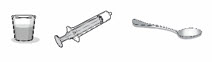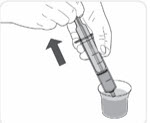 DRUG LABEL: VIJOICE
NDC: 0078-1021 | Form: TABLET
Manufacturer: Novartis Pharmaceuticals Corporation
Category: prescription | Type: HUMAN PRESCRIPTION DRUG LABEL
Date: 20251104

ACTIVE INGREDIENTS: ALPELISIB 50 mg/1 1
INACTIVE INGREDIENTS: CELLULOSE, MICROCRYSTALLINE; MANNITOL; SODIUM STARCH GLYCOLATE TYPE A POTATO; HYPROMELLOSE, UNSPECIFIED; MAGNESIUM STEARATE; TALC; POLYETHYLENE GLYCOL 4000; TITANIUM DIOXIDE; FERRIC OXIDE RED; FERRIC OXIDE YELLOW

HIGHLIGHTS OF PRESCRIBING INFORMATION

These highlights do not include all the information needed to use VIJOICE safely and effectively. See full prescribing information for VIJOICE.
VIJOICE® (alpelisib) tablets, for oral use
VIJOICE® (alpelisib) oral granules
Initial U.S. Approval: 2019

RECENT MAJOR CHANGES

Dosage and Administration, VIJOICE Preparation and Administration Instructions (2.4) | 7/2025
Warnings and Precautions, Severe Hypersensitivity (5.1) | 7/2025

1 INDICATIONS AND USAGE

VIJOICE is a kinase inhibitor indicated for the treatment of adult and pediatric patients 2 years of age and older with severe manifestations of PIK3CA-Related Overgrowth Spectrum (PROS) who require systemic therapy.

This indication is approved under accelerated approval based on response rate and duration of response. Continued approval for this indication may be contingent upon verification and description of clinical benefit in a confirmatory trial(s). (1)

2 DOSAGE AND ADMINISTRATION

Recommended Dose:

- Pediatric patients (2 to less than 18 years of age): 50 mg taken orally once daily with food. (2.1)
- Adult patients: 250 mg taken orally once daily with food. (2.1)

Administration:

- Swallow tablets whole. Do not chew, divide, or crush. (2.4)
- For patients who cannot swallow tablets whole, use tablets or oral granules to create a suspension or a mixture. (2.4)
- VIJOICE suspension made with water can be administered orally or via a nasogastric or gastric tube. (2.4)

See full prescribing information for preparation and administration instructions.

3 DOSAGE FORMS AND STRENGTHS

Tablets: 50 mg, 125 mg, and 200 mg (3)

Oral Granules: 50 mg (3)

4 CONTRAINDICATIONS

Severe hypersensitivity to VIJOICE or to any of its ingredients. (4)

5 WARNINGS AND PRECAUTIONS

- Severe Hypersensitivity: Permanently discontinue VIJOICE. Promptly initiate appropriate treatment. (5.1)
- Severe Cutaneous Adverse Reactions (SCARs): VIJOICE can cause SCARs, including Stevens-Johnson syndrome (SJS), erythema multiforme (EM), toxic epidermal necrolysis (TEN), and drug reaction with eosinophilia and systemic symptoms (DRESS). Interrupt VIJOICE for signs or symptoms of SCARs. Permanently discontinue VIJOICE if SCARs are confirmed. (2.5, 5.2)
- Hyperglycemia: VIJOICE can cause severe hyperglycemia, in some cases associated with hyperglycemic hyperosmolar non-ketotic syndrome (HHNKS) or ketoacidosis. The safety of VIJOICE in patients with Type 1 or uncontrolled Type 2 diabetes has not been established. Before initiating treatment with VIJOICE, test fasting plasma glucose (FPG), HbA1c, and optimize blood glucose. After initiating treatment, monitor periodically. Initiate or optimize anti-hyperglycemic medications as clinically indicated. Interrupt, reduce dose, or discontinue VIJOICE if severe hyperglycemia occurs. (2.5, 5.3)
- Pneumonitis: VIJOICE can cause severe pneumonitis and interstitial lung disease. Monitor for clinical symptoms or radiological changes. Permanently discontinue VIJOICE if pneumonitis occurs. (2.5, 5.4)
- Diarrhea or Colitis: VIJOICE can cause severe diarrhea, resulting in dehydration and in some cases in acute kidney injury, as well as colitis. Monitor for diarrhea and additional symptoms of colitis, including abdominal pain and mucus or blood in stool. Interrupt, reduce dose, or permanently discontinue VIJOICE based on severity of diarrhea or colitis. Patients with colitis may require additional treatment, such as enteric-acting and/or systemic steroids. (2.5, 5.5)
- Embryo-Fetal Toxicity: VIJOICE can cause fetal harm. Advise patients of potential risk to a fetus and to use effective contraception. (5.6, 8.1, 8.3)

6 ADVERSE REACTIONS

Most common adverse reactions (Grades 1 to 4, incidence ≥ 10%) were diarrhea, stomatitis, and hyperglycemia. (6.1)

To report SUSPECTED ADVERSE REACTIONS, contact Novartis Pharmaceuticals Corporation at 1-888-669-6682 or FDA at 1-800-FDA-1088 or www.fda.gov/medwatch.

7 DRUG INTERACTIONS

- CYP3A4 Inducers: Avoid coadministration of VIJOICE with a strong CYP3A4 inducer. Consider an alternative concomitant drug with no or minimal potential to induce CYP3A4. (7.1)
- Breast Cancer Resistance Protein (BCRP) Inhibitors: Avoid the use of BCRP inhibitors in patients treated with VIJOICE. If unable to use alternative drugs, closely monitor for increased adverse reactions. (7.1)

8 USE IN SPECIFIC POPULATIONS

Lactation: Advise not to breastfeed. (8.2)

FULL PRESCRIBING INFORMATION

1 INDICATIONS AND USAGE

VIJOICE is indicated for the treatment of adult and pediatric patients 2 years of age and older with severe manifestations of PIK3CA-Related Overgrowth Spectrum (PROS) who require systemic therapy.

This indication is approved under accelerated approval based on response rate and duration of response. Continued approval for this indication may be contingent upon verification and description of clinical benefit in a confirmatory trial(s).

2 DOSAGE AND ADMINISTRATION

2.1 Recommended Dosage

Adult Patients

The recommended dosage of VIJOICE in adult patients is 250 mg orally, once daily, administered as recommended [see Dosage and Administration (2.2, 2.3, 2.4)] until disease progression or unacceptable toxicity.

Pediatric Patients (2 to less than 18 years of age)

The recommended initial dosage of VIJOICE in pediatric patients is 50 mg orally, once daily, administered as recommended [see Dosage and Administration (2.2, 2.3, 2.4)] until disease progression or unacceptable toxicity.

Consider a dose increase to 125 mg once daily in pediatric patients ≥ 6 years old for response optimization (clinical/radiological) after 24 weeks of treatment with VIJOICE at 50 mg once daily. When a pediatric patient turns 18 years old, consider a gradual dose increase up to 250 mg. Recommended dose increases by age group are listed in Table 1.

Table 1: Recommended Daily VIJOICE Dose Levels for Pediatric Patients (2 to less than 18 years of age)
Patient age (years) | Initial dose | Dose increase
2 to < 6 | 50 mga | Not applicableb
6 to < 18 | 50 mga | 125 mg
aDose can be administered as VIJOICE tablets or VIJOICE oral granules.
bA recommended increased dose has not been established.

2.2 VIJOICE Dosage Form Overview

VIJOICE is available in two dosage forms: tablets and oral granules.

Prescribe the most appropriate dosage form of VIJOICE according to the dose required and patient needs.

VIJOICE Tablets (50 mg, 125 mg, and 200 mg) may be administered as:

- Whole tablets: For patients who can swallow whole tablets.
- Tablets prepared as an oral suspension: For patients who have difficulty swallowing whole tablets [see Dosage and Administration (2.4)].

VIJOICE Oral Granules (50 mg per packet):

- For patients who are prescribed a 50 mg daily dose only [see Dosage and Administration (2.1)].
- Do not use multiple 50 mg packets or a partial packet of oral granules for patients prescribed a 125 mg or a 250 mg dose [see Clinical Pharmacology (12.3)].
- Do not combine VIJOICE tablets and VIJOICE oral granules to achieve the prescribed dose.

2.3 VIJOICE Administration Overview

Take VIJOICE with food at approximately the same time each day [see Clinical Pharmacology (12.3)].

If a dose of VIJOICE is missed, it can be taken with food within 9 hours after the time it is usually taken. After more than 9 hours, skip the dose for that day. The next day, take VIJOICE at the usual time.

If the patient vomits after taking the dose, advise the patient not to take an additional dose on that day, and to resume the dosing schedule the next day at the usual time.

2.4 VIJOICE Preparation and Administration Instructions

VIJOICE Tablets

Swallow VIJOICE tablets whole, or prepare as a suspension to administer orally, or via feeding tubes.

VIJOICE Tablets, Whole

- Swallow VIJOICE tablets whole and take with food. Do not chew, divide, or crush.
- Do not use broken, cracked, or damaged tablets.

VIJOICE Tablets Prepared as a Suspension for Oral use, or Feeding Tubes (Nasogastric or Gastric Tube) Administration

- For patients who are not able to swallow tablets, or who are using a feeding tube, prepare and administer VIJOICE as a suspension and take with food [see Clinical Pharmacology (12.3)].
  - To prepare VIJOICE tablets as a suspension for oral use, place VIJOICE tablets in a cup containing 2 to 4 ounces of water. To prepare VIJOICE tablets as a suspension for feeding tubes administration, place VIJOICE tablets in a cup containing 1 to 2 ounces of water. Make the suspension with water only.
  - Let tablets stand in water for approximately 5 minutes.
  - Crush the tablets with a spoon and stir until a suspension is obtained.
  - Immediately after preparation, administer the suspension as directed below. If not administered immediately after preparation, stir the suspension with the same spoon to re-suspend any particles before administration.
  - Discard the suspension if it is not administered within 60 minutes after preparation.
  Oral Administration
  - Administer the suspension from the cup. After administration of the suspension, add approximately 1 to 2 ounces of water to the same cup. Stir with the same spoon to re-suspend any remaining particles and administer the entire contents of the cup orally. Repeat if particles remain.
  Feeding Tubes Administration
  - Administer VIJOICE tablets prepared as a suspension via French size 5 to 12 diameter silicone or polyurethane nasogastric tubes, or via French size 12 to 24 diameter silicone gastric tubes.
  - Withdraw VIJOICE suspension from the cup into an enteral syringe and administer it via the nasogastric or gastric tube.
  - After administration, add approximately 1 to 2 ounces (approximately 30 to 60 mL) of water to the same cup. Stir with the same spoon to re-suspend any remaining particles. Withdraw the contents of the cup into the same enteral syringe and administer it via the nasogastric or gastric tube. Repeat if particles remain.

VIJOICE Oral Granules

Administer VIJOICE oral granules directly onto the tongue with water, or prepare as a suspension or a mixture for oral use. To administer via feeding tubes prepare the suspension with water only.

- Each packet is for single use only.
- No packet should be used if the packet seal is broken.
- Do not attempt to use partial quantities of oral granules from 50 mg granules packets to prepare a dose. Do not combine VIJOICE tablets and VIJOICE oral granules to achieve the prescribed dose of 125 mg or 250 mg.
- For patients for whom a daily dose of 50 mg is prescribed, administer VIJOICE oral granules [see Clinical Pharmacology (12.3)] in one of the following ways:

VIJOICE Oral Granules for Direct Oral Administration

- Pour the contents of one VIJOICE oral granules packet directly onto the tongue and swallow with approximately 2 to 4 ounces of water. If needed, rinse the mouth with additional water and swallow to ensure no particles remain in the mouth.

VIJOICE Oral Granules as a Suspension or a Mixture for Oral administration

- Pour the contents of one VIJOICE oral granules packet into a cup.
- Add 1 to 3 teaspoons (about 0.5 ounces) of a beverage (water, milk, or apple juice) or soft food (applesauce or yogurt) and stir with a spoon, then administer the suspension or the mixture immediately.
- Rinse the cup with up to 2 ounces of a beverage (water, milk or apple juice) and administer the rinse immediately to ensure the entire dose is administered. If particles remain, repeat until the full dose is administered.
- If not administered immediately after preparation, stir the suspension or the mixture with the same spoon to re-suspend any particles before administration.
- Discard the oral granules mixed with water, milk, apple juice, applesauce, or yogurt if they are not administered within 60 minutes after preparation.

VIJOICE Oral Granules Suspension for Feeding Tubes Administration

For patients who are not able to swallow VIJOICE orally, administer VIJOICE via feeding tubes.

Administer VIJOICE granules via French size 8 to 12 diameter silicone or polyurethane nasogastric tubes or via French size 12 to 24 diameter silicone gastric tubes.

- Pour the contents of one VIJOICE granules packet into a cup.
- Add 4 teaspoons (about 0.7 ounces or 20 mL) of water and stir gently with a spoon until a suspension is obtained. Make the suspension with water only.
- Immediately after preparation, withdraw the suspension from the cup into an enteral syringe and administer it via the nasogastric or gastric tube.
- After administration, add 4 teaspoons (about 0.7 ounces or 20 mL) of water to the same cup. Stir with the same spoon to re-suspend any remaining particles. Withdraw the contents of the cup into the same enteral syringe and administer it via the nasogastric or gastric tube. Repeat if particles remain.
- If not administered immediately after preparation, stir the suspension with the same spoon to re-suspend any particles before withdrawing into an enteral syringe for administration.
- Discard the suspension if it is not administered within 60 minutes after preparation.

2.5 Dosage Modifications for Adverse Reactions

The recommended VIJOICE dose reductions for adverse reactions in adult and pediatric patients are listed in Table 2 and Table 3, respectively.

Table 2: VIJOICE Dosage Reduction Recommendations for Adverse Reactions in Adult Patients
VIJOICE dose level | Dose and schedule
First-dose reduction | 125 mg once daily
Second-dose reduction | 50 mg once dailya
aDose can be administered as VIJOICE tablets or VIJOICE oral granules.

Table 3: VIJOICE Dosage Reduction Recommendations for Adverse Reactions in Pediatric Patients
Action | VIJOICE dose prior to dose reduction
 | 125 mg once daily | 50 mg once daily
Dose reduction | 50 mg once dailya | Not applicable
aDose can be administered as VIJOICE tablets or VIJOICE oral granules.

Discontinue VIJOICE in adults or pediatric patients who cannot tolerate 50 mg daily.

Tables 4, 5, 6, 7, 8, and 9 summarize recommendations for dose interruption, reduction, or discontinuation of VIJOICE in the management of specific adverse reactions.

Cutaneous Adverse Reactions

If a severe cutaneous adverse reaction (SCAR) is confirmed, permanently discontinue VIJOICE. Do not reintroduce VIJOICE in patients who have experienced previous SCAR during VIJOICE treatment [see Warnings and Precautions (5.2)].

Table 4: Dosage Modification and Management for Rash and Severe Cutaneous Adverse Reactions (SCARs)
[see Warnings and Precautions (5.1, 5.2)]
Gradea,b | Recommendation for adult and pediatric patientsc
Grade 1 (< 10% body surface area [BSA] with active skin toxicity) | No VIJOICE dosage modification is required unless the etiology is determined to be SCAR. Initiate topical corticosteroid treatment. Consider adding oral antihistamine to manage symptoms. If active rash is not improved within 28 days of appropriate treatment, add a low dose systemic corticosteroid. If the etiology is determined to be SCAR, permanently discontinue VIJOICE.
Grade 2 (10% to 30% BSA with active skin toxicity) | No VIJOICE dosage modification is required unless the etiology is determined to be SCAR. Initiate or intensify topical corticosteroid and oral antihistamine treatment. Consider low dose systemic corticosteroid treatment. If rash improves to Grade ≤ 1 within 10 days, systemic corticosteroid may be discontinued. If the etiology is determined to be SCAR, permanently discontinue VIJOICE.
Grade 3 (e.g., severe rash not responsive to medical management) (> 30% BSA with active skin toxicity) | Interrupt VIJOICE and initiate or intensify topical/systemic corticosteroid and oral antihistamine treatment. If the etiology is determined to be SCAR, permanently discontinue VIJOICE. For rashes other than SCAR Adult Patients:; - Upon improvement to Grade ≤ 1, resume VIJOICE at the next lower dose level.; Pediatric Patients:; - Upon improvement to Grade ≤ 1, either resume VIJOICE at 50 mg while continuing oral antihistamine treatment or permanently discontinue VIJOICE. - Permanently discontinue VIJOICE if: - Patient was receiving antihistamines at the time of rash onset and antihistamine dose cannot be increased - Grade ≥ 3 rash recurs
Grade 4 (e.g., severe bullous, blistering or exfoliating skin conditions) (any % BSA associated with extensive superinfection, with IV antibiotics indicated; life-threatening consequences) | Permanently discontinue VIJOICE.
aGrading according to Common Terminology Criteria for Adverse Events (CTCAE) Version 5.0.
bFor all grades of rash, consider consultation with a dermatologist.
cAntihistamines administered prior to rash onset may decrease incidence and severity of rash.

Hyperglycemia

Before initiating treatment with VIJOICE, test fasting plasma glucose (FPG), HbA1c, and optimize blood glucose. After initiating treatment with VIJOICE, monitor fasting glucose (FPG or fasting blood glucose) at least once every week for the first 2 weeks, then at least once every 4 weeks, and as clinically indicated. Monitor HbA1c every 3 months and as clinically indicated. In patients with risk factors for hyperglycemia, monitor fasting glucose more closely and as clinically indicated [see Warnings and Precautions (5.3)].

Table 5: Dosage Modification and Management for Hyperglycemia
[see Warnings and Precautions (5.3)]
Fasting plasma glucose (FPG)/Fasting blood glucose valuesa | Recommendation for adult and pediatric patients
Dose modifications and management should only be based on fasting glucose values (FPG or fasting blood glucose).
Grade 1 Fasting glucose > ULN -160 mg/dL or > ULN -8.9 mmol/L | No VIJOICE dosage modification is required. Initiate or intensify oral anti-hyperglycemic treatmentb.
Grade 2 Fasting glucose > 160 - 250 mg/dL or > 8.9 - 13.9 mmol/L | No VIJOICE dosage modification is required. Initiate or intensify oral anti-hyperglycemic treatmentb. Adult Patients:; - If fasting glucose does not decrease to ≤ 160 mg/dL or 8.9 mmol/L within 21 days under appropriate anti-hyperglycemic treatmentb, reduce VIJOICE dose by 1 dose level and follow fasting glucose value-specific recommendations.; Pediatric Patients:; - If fasting glucose does not decrease to ≤ 160 mg/dL or 8.9 mmol/L within 21 days under appropriate anti-hyperglycemic treatmentb, interrupt VIJOICE until improvement to Grade ≤ 1, then resume VIJOICE at 50 mg and follow fasting glucose value-specific recommendations.
Grade 3 Fasting glucose > 250 - 500 mg/dL or > 13.9 - 27.8 mmol/L | Interrupt VIJOICE. Initiate or intensify oral anti-hyperglycemic treatmentb and consider additional anti-hyperglycemic medications for 1-2 days until hyperglycemia improves, as clinically indicated. Administer intravenous hydration and consider appropriate treatment (e.g., intervention for electrolyte/ketoacidosis/hyperosmolar disturbances). Adult Patients:; - If fasting glucose decreases to ≤ 160 mg/dL or 8.9 mmol/L within 3 to 5 days under appropriate anti-hyperglycemic treatment, resume VIJOICE at 1 lower dose level. - If fasting glucose does not decrease to ≤ 160 mg/dL or 8.9 mmol/L within 3 to 5 days under appropriate anti-hyperglycemic treatment, consultation with a physician with expertise in the treatment of hyperglycemia is recommended. - If fasting glucose does not decrease to ≤ 160 mg/dL or 8.9 mmol/L within 21 days following appropriate anti-hyperglycemic treatmentb, permanently discontinue VIJOICE.; Pediatric Patients:; - If fasting glucose decreases to ≤ 160 mg/dL or 8.9 mmol/L within 3 to 5 days under appropriate anti-hyperglycemic treatment, resume VIJOICE at 50 mg. - If fasting glucose does not decrease to ≤ 160 mg/dL or 8.9 mmol/L within 3 to 5 days under appropriate anti-hyperglycemic treatment, consultation with a physician with expertise in the treatment of hyperglycemia is recommended to determine if treatment with VIJOICE should be resumed or permanently discontinued. - If fasting glucose does not decrease to ≤ 160 mg/dL or 8.9 mmol/L within 21 days following appropriate anti-hyperglycemic treatmentb, permanently discontinue VIJOICE. - If hyperglycemia recurs at Grade ≥ 3, consider permanent discontinuation of VIJOICE.
Grade 4 Fasting glucose > 500 mg/dL or > 27.8 mmol/L | Interrupt VIJOICE. Initiate or intensify appropriate oral anti-hyperglycemic treatmentb. Administer intravenous hydration and consider appropriate treatment (e.g., intervention for electrolyte/ketoacidosis/hyperosmolar disturbances). Re-check fasting glucose within 24 hours and as clinically indicated.; - If fasting glucose decreases to ≤ 500 mg/dL or 27.8 mmol/L, follow fasting glucose value-specific recommendations for Grade 3. - If fasting glucose is confirmed at > 500 mg/dL or 27.8 mmol/L, permanently discontinue VIJOICE.
Abbreviation: ULN, upper limit of normal.
aFPG/Fasting Blood Glucose/Grade levels reflect hyperglycemia grading according to Common Terminology Criteria for Adverse Events (CTCAE) Version 4.03.
bInitiate applicable anti-hyperglycemic medications, including metformin in adult and pediatric patients ≥ 10 years, SGLT2 inhibitors or insulin sensitizers (such as thiazolidinediones or dipeptidyl peptidase-4 inhibitors) in adult patients, and review respective prescribing information for dosing and dose titration recommendations, including local hyperglycemic treatment guidelines [see Warnings and Precautions (5.3)].

Pneumonitis

Table 6: Dosage Modification for Pneumonitis
[see Warnings and Precautions (5.4)]
Gradea | Recommendation for adult and pediatric patients
Any Grade | • Interrupt VIJOICE if pneumonitis is suspected. • Permanently discontinue VIJOICE if pneumonitis is confirmed.
aGrading according to CTCAE Version 5.0.

Diarrhea or Colitis

In pediatric patients, consider consultation with a physician with experience in the treatment of gastrointestinal conditions.

Table 7: Dosage Modification and Management for Diarrhea or Colitis
[see Warnings and Precautions (5.5)]
Gradea | Recommendation for adult and pediatric patients
Grade 1 | No VIJOICE dosage modification is required. Initiate appropriate medical therapy and monitor as clinically indicated.
Grade 2 | Interrupt VIJOICE dose until improvement to Grade ≤ 1, then resume VIJOICE at the same dose level. Initiate or intensify appropriate medical therapy and monitor as clinically indicatedb. Adult Patients:; - For recurrent Grade ≥ 2, interrupt VIJOICE dose until improvement to Grade ≤ 1, then resume VIJOICE at the next lower dose level.; Pediatric Patients:; - For recurrent Grade ≥ 2, interrupt VIJOICE dose until improvement to Grade ≤ 1, then resume VIJOICE at 50 mg.
Grade 3 | Interrupt VIJOICE dose until improvement to Grade ≤ 1. Initiate or intensify appropriate medical therapy and monitor as clinically indicatedb. Adult Patients:; - Once improved to Grade ≤ 1, then resume VIJOICE at the next lower dose level.; Pediatric Patients:; - Once improved to Grade ≤ 1, either resume VIJOICE at 50 mg or permanently discontinue VIJOICE. - For recurrent Grade ≥ 3, consider permanent discontinuation of VIJOICE.
Grade 4 | Permanently discontinue VIJOICE.
aGrading according to CTCAE Version 5.0.
bFor Grade 2 and 3 colitis consider additional treatment, such as enteric-acting and/or systemic steroids.

Pancreatitis

Table 8: Dosage Modification for Pancreatitis
Gradea | Recommendation for adult and pediatric patients
Grade 2 | Interrupt VIJOICE dose until improvement to Grade < 2. Adult Patients:; - Resume VIJOICE at the next lower dose level (only one dose reduction is permitted). - If pancreatitis recurs, permanently discontinue VIJOICE.; Pediatric Patients:; - Resume VIJOICE at 50 mg. - If pancreatitis recurs, permanently discontinue VIJOICE.
Grade 3 | Adult Patients:; - Interrupt VIJOICE dose until improvement to Grade < 2. - Resume VIJOICE at the next lower dose level (only one dose reduction is permitted). - If pancreatitis recurs, permanently discontinue VIJOICE.; Pediatric Patients:; - Permanently discontinue VIJOICE.
Grade 4 | Permanently discontinue VIJOICE.
aGrading according to CTCAE Version 5.0.

Other Adverse Reactions

Table 9: Dosage Modification and Management for Other Adverse Reactions (Excluding Rash and Severe Cutaneous Adverse Reactions, Hyperglycemia, Pneumonitis, Diarrhea or Colitis, and Pancreatitis)
Gradea | Recommendation for adult and pediatric patients
Grade 1 or 2b,c,d | No VIJOICE dosage modification is required. Initiate appropriate medical therapy and monitor as clinically indicatedb,c,d.
Grade 3 | Interrupt VIJOICE dose until improvement to Grade ≤ 1. Initiate or intensify appropriate medical therapy and monitor as clinically indicated. Adult Patients:; - Once improved to Grade ≤ 1, then resume VIJOICE at the next lower dose level.; Pediatric Patients:; - Once improved to Grade ≤ 1, either resume VIJOICE at 50 mg or permanently discontinue VIJOICE. - If adverse reaction recurs at Grade ≥ 3, consider permanent discontinuation of VIJOICE. - Consider consultation with a qualified physician with specific expertise in the field of the concerned adverse reaction.
Grade 4 | Permanently discontinue VIJOICE.
aGrading according to CTCAE Version 5.0.
bFor Grade 2 total bilirubin elevation in adult patients, interrupt VIJOICE dose until improvement to Grade ≤ 1. If improvement occurs in ≤ 14 days, resume at the same dose level. If improvement occurs in > 14 days, resume VIJOICE at the next lower dose level.
cFor Grade 2 total bilirubin elevation in pediatric patients, interrupt VIJOICE dose until improvement to Grade ≤ 1. If improvement occurs in ≤ 14 days, resume at the same dose level. If improvement occurs in > 14 days, resume VIJOICE at 50 mg.
dIf alopecia becomes a concern, consider consulting a dermatologist.

3 DOSAGE FORMS AND STRENGTHS

Tablets

50 mg: Light yellow, unscored, round and curved with beveled edges film-coated tablet, debossed with “C7” on one side and “NVR” on the other side.

125 mg: Dark yellow, unscored, ovaloid and curved with beveled edges film-coated tablet, debossed with “Y7” on one side and “NVR” on the other side.

200 mg: Pale yellow, unscored, ovaloid and curved with beveled edges film-coated tablet, debossed with “CL7” on one side and “NVR” on the other side.

Oral Granules

50 mg: White to almost white free flowing mixture of powder and granules in packets.

4 CONTRAINDICATIONS

VIJOICE is contraindicated in patients with severe hypersensitivity to alpelisib or any of its ingredients [see Warnings and Precautions (5.1)].

5 WARNINGS AND PRECAUTIONS

5.1 Severe Hypersensitivity

Severe hypersensitivity reactions, including anaphylaxis, anaphylactic shock, and angioedema, have occurred in adult patients treated with alpelisib in the oncology setting and in patients treated with VIJOICE [see Adverse Reactions (6.1)]. VIJOICE is not approved for use in the oncology setting.

Permanently discontinue VIJOICE in the event of severe hypersensitivity [see Contraindications (4)].

5.2 Severe Cutaneous Adverse Reactions

Severe cutaneous adverse reactions (SCARs), including Stevens-Johnson syndrome (SJS), erythema multiforme (EM), toxic epidermal necrolysis (TEN), and drug reaction with eosinophilia and systemic symptoms (DRESS), have occurred in adult patients treated with alpelisib in the oncology setting and may occur in patients treated with VIJOICE. VIJOICE is not approved for use in the oncology setting.

If signs or symptoms of SCARs occur, interrupt VIJOICE until the etiology of the reaction has been determined. Consultation with a dermatologist is recommended.

If a SCAR is confirmed, permanently discontinue VIJOICE.

If a SCAR is not confirmed, VIJOICE may require dose modifications, topical or systemic corticosteroids, or oral antihistamine treatment as described in Table 4 [see Dosage and Administration (2.5)].

5.3 Hyperglycemia

Severe hyperglycemia, in some cases associated with hyperglycemic hyperosmolar non-ketotic syndrome (HHNKS) or fatal cases of ketoacidosis, has occurred in adult patients treated with alpelisib in the oncology setting and may occur in patients treated with VIJOICE. VIJOICE is not approved for use in the oncology setting.

In the EPIK-P1 study, Grade 1 or 2 hyperglycemia was reported in 12% of patients treated with VIJOICE [see Adverse Reactions (6.1)].

Before initiating treatment with VIJOICE, test fasting plasma glucose (FPG), HbA1c, and optimize blood glucose. After initiating treatment with VIJOICE, monitor fasting glucose (FPG or fasting blood glucose) at least once every week for the first 2 weeks, then at least once every 4 weeks, and as clinically indicated. Monitor HbA1c every 3 months and as clinically indicated. Monitor fasting glucose more frequently for the first few weeks during treatment with VIJOICE in patients with risk factors for hyperglycemia, such as obesity (BMI ≥ 30), elevated FPG, HbA1c at the upper limit of normal or above, use of concomitant systemic corticosteroids, or age ≥ 75 [see Use in Specific Populations (8.5)].

If a patient experiences hyperglycemia after initiating treatment with VIJOICE, monitor fasting glucose as clinically indicated, and at least twice weekly until fasting glucose decreases to normal levels. During treatment with anti-hyperglycemic medication, continue monitoring fasting glucose at least once a week for 8 weeks, followed by once every 2 weeks and as clinically indicated. Consider consultation with a healthcare practitioner with expertise in the treatment of hyperglycemia and counsel patients on lifestyle changes.

The safety of VIJOICE in patients with Type 1 and uncontrolled Type 2 diabetes has not been established. Patients with a history of diabetes mellitus may require intensified hyperglycemic treatment. Closely monitor patients with diabetes.

Interrupt, reduce the dose, or permanently discontinue VIJOICE based on the severity as described in Table 5 [see Dosage and Administration (2.5)].

5.4 Pneumonitis

Severe pneumonitis, including acute interstitial pneumonitis and interstitial lung disease, has occurred in adult patients treated with alpelisib in the oncology setting and may occur in patients treated with VIJOICE. VIJOICE is not approved for use in the oncology setting.

In patients who have new or worsening respiratory symptoms or are suspected to have developed pneumonitis, interrupt VIJOICE immediately and evaluate the patient for pneumonitis. Consider a diagnosis of non-infectious pneumonitis in patients presenting with non-specific respiratory signs and symptoms, such as hypoxia, cough, dyspnea, or interstitial infiltrates on radiologic exams and in whom infectious, neoplastic, and other causes have been excluded by means of appropriate investigations.

Permanently discontinue VIJOICE in all patients with confirmed pneumonitis [see Dosage and Administration (2.5)].

5.5 Diarrhea or Colitis

Severe diarrhea, resulting in dehydration and in some cases in acute kidney injury, as well as colitis, have occurred in adult patients treated with alpelisib in the oncology setting and may occur in patients treated with VIJOICE. VIJOICE is not approved for use in the oncology setting.

In the EPIK-P1 study, 16% of patients experienced Grade 1 diarrhea during treatment with VIJOICE [see Adverse Reactions (6.1)].

Monitor patients for diarrhea and additional symptoms of colitis, such as abdominal pain and mucus or blood in stool. Interrupt, reduce the dose or permanently discontinue VIJOICE based on the severity of diarrhea or colitis [see Dosage and Administration (2.5)].

Patients with colitis may require additional treatment, such as enteric-acting and/or systemic steroids [see Dosage and Administration (2.5)].

5.6 Embryo-Fetal Toxicity

Based on findings in animals and its mechanism of action, VIJOICE can cause fetal harm when administered to a pregnant woman. In animal reproduction studies, oral administration of alpelisib to pregnant animals during organogenesis caused adverse developmental outcomes, including embryo-fetal mortality (post-implantation loss), reduced fetal weights, and increased incidences of fetal malformations at doses that were approximately equivalent to the recommended pediatric and adult doses. Advise pregnant women and females of reproductive potential of the potential risk to a fetus. Advise females of reproductive potential to use effective contraception during treatment with VIJOICE and for 1 week after the last dose. Advise male patients with female partners of reproductive potential to use condoms and effective contraception during treatment with VIJOICE and for 1 week after the last dose [see Use in Specific Populations (8.1, 8.3) and Clinical Pharmacology (12.1)].

6 ADVERSE REACTIONS

The following clinically significant adverse reactions are discussed elsewhere in the labeling:

- Severe Hypersensitivity [see Warnings and Precautions (5.1)]
- Severe Cutaneous Adverse Reactions [see Warnings and Precautions (5.2)]
- Hyperglycemia [see Warnings and Precautions (5.3)]
- Pneumonitis [see Warnings and Precautions (5.4)]
- Diarrhea or Colitis [see Warnings and Precautions (5.5)]

6.1 Clinical Trial Experience

Because clinical trials are conducted under widely varying conditions, adverse reaction rates observed in the clinical trials of a drug cannot be directly compared to rates in the clinical trials of another drug and may not reflect the rates observed in practice.

The safety of VIJOICE was evaluated in EPIK-P1 (NCT04285723), a single-arm clinical study in patients who were treated as part of an expanded access program for compassionate use. Fifty-seven patients 2 years of age and older with severe or life-threatening PIK3CA-Related Overgrowth Spectrum (PROS) received VIJOICE based on age at dosages ranging from 50 mg to 250 mg orally once daily [see Clinical Studies (14)]. Among patients who received VIJOICE, 95% were exposed for 6 months or longer and 79% were exposed for greater than one year.

The median age of patients who received VIJOICE was 14 years (range, 2 to 50); 58% were female; 12% were White and race was not reported for 88%.

Serious adverse reactions occurred in 12% of patients who received VIJOICE. Serious adverse reactions occurring in two or more patients included dehydration (n = 2) and cellulitis (n = 2).

Dosage interruption of VIJOICE due to an adverse reaction occurred in 11% of patients. Adverse reactions which required dosage interruption in two or more patients included dizziness (n = 2) and vomiting (n = 2). Dose reductions of VIJOICE due to an adverse reaction occurred in 5% of patients. Adverse reactions which required dose reduction included alopecia, memory impairment, and soft tissue infection.

The most common adverse reactions (≥ 10%) were diarrhea, stomatitis, and hyperglycemia. The most common Grade 3 or 4 laboratory abnormalities (≥ 2%) were increased glucose, decreased hemoglobin, decreased phosphate, increased bilirubin, decreased sodium, and decreased platelets.

Adverse reactions and laboratory abnormalities are listed in Table 10 and Table 11, respectively.

Table 10: Adverse Reactions (≥ 5%) in Patients with PROS Who Received VIJOICE in EPIK-P1
 | VIJOICE N = 57
Adverse reactions
 | All Grades (%) | Grade 3 or 4 (%)
Gastrointestinal disorders
Diarrhea | 16 | 0
Stomatitisa | 16 | 0
Metabolism and nutrition disorders
Hyperglycemia | 12 | 0
Skin and subcutaneous tissue disorders
Eczema | 7 | 0
Dry skin | 7 | 0
Alopecia | 5 | 0
Nervous system disorders
Headache | 5 | 0
Infections and infestations
Cellulitis | 5 | 3.5
Grading according to CTCAE Version 4.03.
aStomatitis: including stomatitis and aphthous ulcer.

Clinically relevant adverse reactions in < 5% of patients who received VIJOICE included nausea, vomiting, dehydration, and mucosal dryness.

Table 11: Laboratory Abnormalities Worsening from Baseline in ≥ 10% of Patients with PROS Who Received VIJOICE in EPIK-P1
Laboratory abnormality | VIJOICEa N = 57
 | All Grades % | Grade 3 or 4 %
Chemistry
Decreased calcium (corrected) | 60 | 0
Decreased phosphate | 59 | 5b
Increased glucosec | 56 | 11b
Increased glycosylated hemoglobin (HbA1c)d | 38d | N/Ad
Increased creatinine | 31 | 0
Increased bilirubin | 29 | 2b
Increased potassium | 24 | 0
Increased triglycerides | 19 | 0
Decreased magnesium | 18 | 0
Increased aspartate aminotransferase (AST) | 17 | 0
Increased cholesterol | 13 | 0
Decreased albumin | 13 | 0
Decreased sodium | 12 | 2b
Decreased potassium | 12 | 0
Increased gamma glutamyl transferase (GGT) | 11 | 0
Increased alanine aminotransferase (ALT) | 10 | 0
Hematology
Decreased leukocyte | 22 | 0
Decreased hemoglobin | 20 | 6b
Decreased lymphocyte | 20 | 0
Decreased neutrophil | 19 | 0
Increased lymphocyte | 17 | 0
Decreased platelets | 14 | 2b
Grading according to CTCAE Version 4.03.
Abbreviation: N/A, not available.
aThe denominator used to calculate the rate varied from 9 to 50 based on the number of patients with a baseline value and at least one post-treatment value.
bNo Grade 4 laboratory abnormalities were reported.
cGlucose increase is an expected laboratory abnormality of PI3K inhibition.
dNo CTCAE grade available. For HbA1c, baseline values increasing post-treatment to a value above the upper limit of the normal range (≥ 5.7%) are considered increased.

Other Clinical Trials Experience

The following additional adverse reactions and laboratory abnormality have been identified following administration of VIJOICE: hypersensitivity, lipase increased, dermatitis, and abdominal pain.

6.2 Postmarketing Experience and Other Spontaneous Adverse Reaction Reports

The following adverse reactions have been identified with VIJOICE use in patients with PROS in an expanded access program for compassionate use. Because these reactions are reported from a population of uncertain size, it is not always possible to reliably estimate their frequency or establish a causal relationship to drug exposure.

Metabolism and nutrition disorders: Decreased appetite.

Skin and subcutaneous tissue disorders: Pruritus, rash (including rash maculo-papular, rash erythematous, rash papular, and rash pruritic), acne (including dermatitis acneiform).

7 DRUG INTERACTIONS

7.1 Effect of Other Drugs on VIJOICE

CYP3A4 Inducers

Avoid coadministration of VIJOICE with strong CYP3A4 inducers and consider an alternative concomitant drug with no or minimal potential to induce CYP3A4.

Alpelisib is metabolized by CYP3A4. Concomitant use of VIJOICE with a strong CYP3A4 inducer may decrease alpelisib concentration [see Clinical Pharmacology (12.3)], which may decrease alpelisib activity.

Breast Cancer Resistance Protein Inhibitors (BCRP)

Avoid the use of BCRP inhibitors in patients treated with VIJOICE. If unable to use alternative drugs, when VIJOICE is used in combination with BCRP inhibitors, closely monitor for increased adverse reactions.

Alpelisib is transported by BCRP. Concomitant use of VIJOICE with a BCRP inhibitor may increase alpelisib exposure [see Clinical Pharmacology (12.3)], which may increase the risk of adverse reactions.

8 USE IN SPECIFIC POPULATIONS

8.1 Pregnancy

Risk Summary

Based on animal data and mechanism of action, VIJOICE can cause fetal harm when administered to a pregnant woman [see Clinical Pharmacology (12.1)]. There are no available data in pregnant women to inform the drug-associated risk. In animal reproduction studies, oral administration of alpelisib to pregnant rats and rabbits during organogenesis caused adverse developmental outcomes, including embryo-fetal mortality (post-implantation loss), reduced fetal weights, and increased incidences of fetal malformations at doses described below (see Data). Advise pregnant women of the potential risk to a fetus.

The estimated background risk of major birth defects and miscarriage for the indicated population is unknown. However, the estimated background risk of major birth defects is 2% to 4% and of miscarriage is 15% to 20% of clinically recognized pregnancies in the U.S. general population.

Data

Animal Data

In embryo-fetal development studies in rats and rabbits, pregnant animals received oral doses of alpelisib during the period of organogenesis. In the rat study, animals were dosed at 3, 10, or 30 mg/kg/day from gestation day 6 to 17; and in the rabbit study, animals were dosed at 3, 15, 25, and 30 mg/kg/day from gestation day 7 to 20.

In rats, oral administration of alpelisib resulted in maternal toxicity (body weight loss, low food consumption) and no viable fetuses (post-implantation loss) at 30 mg/kg/day (approximately 3.6 to 1.2 times the initial recommended doses of 50 mg and 250 mg in pediatric and adult patients, respectively, based on BSA). At a dose of 10 mg/kg/day (approximately 1.2 to 0.4 times the initial recommended doses of 50 mg and 250 mg in pediatric and adult patients, respectively, based on BSA), toxicities included reduced fetal weight and increased incidences of skeletal malformations (bent scapula and thickened or bent long bones) and fetal variations (enlarged brain ventricle, decreased bone ossification).

In a pilot embryo-fetal development study in rabbits, a dose of 30 mg/kg/day (approximately 7 to 2.2 times the initial recommended doses of 50 mg and 250 mg in pediatric and adult patients based on BSA) resulted in no viable fetuses (post-implantation loss). Doses ≥ 15 mg/kg/day (approximately 3.5 to 1.1 times the initial recommended doses of 50 mg and 250 mg in pediatric and adult patients, respectively, based on BSA) resulted in increased embryo-fetal deaths, reduced fetal weights, and malformations, mostly related to the tail and head.

8.2 Lactation

Risk Summary

There are no data on the presence of alpelisib in human milk, its effects on milk production, or the breastfed child. Because of the potential for serious adverse reactions in the breastfed child, advise lactating women to not breastfeed during treatment with VIJOICE and for 1 week after the last dose.

8.3 Females and Males of Reproductive Potential

Pregnancy Testing

Verify the pregnancy status in females of reproductive potential prior to initiating VIJOICE.

Contraception

Females

VIJOICE can cause fetal harm when administered to a pregnant woman [see Use in Specific Populations (8.1)]. Advise females of reproductive potential to use effective contraception during treatment with VIJOICE and for 1 week after the last dose.

Males

Advise male patients with female partners of reproductive potential to use condoms and effective contraception during treatment with VIJOICE and for 1 week after the last dose.

Infertility

Based on findings from animal studies, VIJOICE may impair fertility in males and females of reproductive potential [see Nonclinical Toxicology (13.1)].

8.4 Pediatric Use

The safety and effectiveness of VIJOICE have been established in pediatric patients 2 to less than 18 years of age with PROS based on results from a single-arm clinical study of VIJOICE (EPIK-P1) that enrolled 39 pediatric patients: 11 patients aged 2 to 5 years, 12 patients aged 6 to 11 years, and 16 patients aged 12 to less than 18 years of age [see Adverse Reactions (6.1) and Clinical Studies (14)].

The safety and effectiveness of VIJOICE in pediatric patients below the age of 2 years have not been established.

Although there were no new safety signals observed in pediatric patients, there is insufficient data to determine whether VIJOICE has an adverse impact on growth and development in pediatric patients with PROS. Based on the animal toxicity data (described below), regular monitoring of growth and development in pediatric patients treated with VIJOICE is recommended.

Animal Toxicity Data

In a 4-week general toxicology study, rats administered alpelisib had growth plate thickening and decreased trabeculae of the knee joint, dentin thinning, and degenerative odontoblasts at the dose of 30 mg/kg/day (approximately 2.8 to 1.2 times the initial recommended doses of 50 mg and 250 mg in pediatric and adult patients, respectively, based on BSA). Dentin thinning/irregular dentin was also observed in the 13-week toxicology study in rats at the high dose of 20 mg/kg/day (approximately 2 to 0.8 times the initial recommended doses of 50 mg and 250 mg in pediatric and adult patients, respectively, based on BSA).

8.5 Geriatric Use

There were no adult patients aged 65 years of age or older who received VIJOICE in EPIK-P1.

10 OVERDOSAGE

There is limited experience of overdose with alpelisib in clinical trials.

In cases where accidental overdosage of alpelisib was reported in the clinical studies, the adverse reactions associated with the overdose were consistent with the known safety profile of alpelisib and included hyperglycemia, nausea, asthenia, and rash.

Initiate general symptomatic and supportive measures in all cases of overdosage where necessary. There is no known antidote for VIJOICE.

11 DESCRIPTION

VIJOICE (alpelisib) is a kinase inhibitor. The chemical name of alpelisib is (2S)-N^1-[4-Methyl-5-[2-(2,2,2-trifluoro-1,1-dimethylethyl)-4-pyridinyl]-2-thiazolyl]-1,2-pyrrolidinedicarboxamide. Alpelisib is a white to almost white powder. The molecular formula for alpelisib is C19H22F3N5O2S and the relative molecular mass is 441.47 g/mol. The pH of a 1.0% (m/V) solution of alpelisib in water/ethanol (50:50 V/V) is approximately 6.2. The chemical structure of alpelisib is shown below:

VIJOICE film-coated tablets are supplied for oral administration with three strengths that contain 50 mg, 125 mg, and 200 mg of alpelisib. The tablets also contain hypromellose, magnesium stearate, mannitol, microcrystalline cellulose, and sodium starch glycolate. The film-coating contains hypromellose, iron oxide red (applicable only to 50 mg and 200 mg strengths), iron oxide yellow, macrogol/polyethylene glycol (PEG) 4000, talc, and titanium dioxide.

VIJOICE oral granules are supplied for oral administration with one strength that contains 50 mg of alpelisib. The granules also contain hypromellose, magnesium stearate, mannitol, microcrystalline cellulose, and sodium starch glycolate.

12 CLINICAL PHARMACOLOGY

12.1 Mechanism of Action

Alpelisib is an inhibitor of phosphatidylinositol-3-kinase (PI3K) with inhibitory activity predominantly against PI3Kα. Gain-of-function mutations in the gene encoding the catalytic α-subunit of PI3K (PIK3CA) lead to activation of PI3Kα and Akt-signaling, cellular transformation and the generation of tumors in in vitro and in vivo models.

Activating mutations in PIK3CA have been found to induce a spectrum of overgrowths and malformations comprising a wide group of clinically recognizable disorders commonly known as PROS.

In an inducible mouse model of Congenital Lipomatous Overgrowth, Vascular Malformations, Epidermal Nevi, Scoliosis/Skeletal and Spinal syndrome (CLOVES), a phenotype of PROS, alpelisib inhibition of the PI3K pathway resulted in the prevention or improvement of organ abnormalities associated with the disease, depending on when alpelisib treatment was started. These findings were reversed after withdrawal of alpelisib.

12.2 Pharmacodynamics

The exposure-response relationship and time course of pharmacodynamic response for the safety and effectiveness of VIJOICE have not been characterized.

Cardiac Electrophysiology

At a dose of 300 mg, alpelisib does not prolong the QT interval to any clinically relevant extent in the oncology setting. VIJOICE is not approved for use in the oncology setting.

12.3 Pharmacokinetics

The pharmacokinetics of alpelisib has been studied in healthy subjects and adult patients with solid tumors and are presented as mean (% CV) under fed conditions unless otherwise specified. Alpelisib maximum plasma concentration (Cmax) was 277 ng/mL (24%) and area under the curve (AUC) was 2,090 hr*ng/mL (24%) following administration of a single 50 mg dose of VIJOICE. Steady state alpelisib Cmax and AUC increased proportionally over the dose range of 30 mg (0.6 times the lowest approved recommended dosage) to 450 mg (1.8 times the highest approved recommended dosage) under fed conditions. The mean accumulation of alpelisib was 1.3 to 1.5 and steady state plasma concentrations were reached within 3 days following daily dosage.

Absorption

The median time to reach peak plasma concentration (Tmax) ranged between 2.0 to 4.0 hours.

Effect of Food

A high-fat high-calorie (HFHC) meal (985 calories with 58.1 g of fat) increased alpelisib AUC by 73% and Cmax by 84%, and a low-fat low-calorie (LFLC) meal (334 calories with 8.7 g of fat) increased alpelisib AUC by 77% and Cmax by 145% following administration of a single 300 mg dose of alpelisib as tablets. No clinically relevant differences in alpelisib AUC were observed between LFLC and HFHC meals.

No clinically relevant food effect on alpelisib pharmacokinetics was observed after a single 50 mg oral dose of VIJOICE as granules taken with a LFLC meal as compared to that taken under fasted conditions.

No clinically relevant differences in alpelisib Cmax and AUC were observed following administration of a single 50 mg dose of VIJOICE as granules or tablets taken with a LFLC meal.

Distribution

The apparent volume of distribution of alpelisib at steady state is 114 L (46%). Protein binding of alpelisib is 89% and is independent of concentration.

Elimination

The half-life of alpelisib is predicted to be 8 to 9 hours. The clearance of alpelisib is 9.2 L/hr (21%) under fed conditions.

Metabolism

Alpelisib is primarily metabolized by chemical and enzymatic hydrolysis to form its metabolite BZG791 and followed by CYP3A4 mediated hydroxylation.

Excretion

Following a single oral dose of 400 mg (1.6 times the highest approved recommended dosage) radiolabeled alpelisib under fasted condition, 81% of the administered dose was recovered in feces (36% unchanged) and 14% (2% unchanged) in urine. CYP3A4-mediated metabolites (12%) and glucuronides amounted to approximately 15% of the dose.

Specific Populations

No clinically significant differences in the pharmacokinetics of alpelisib were predicted based on age (21 to 87 years), sex, race/ethnicity (Japanese or Caucasian), body weight (37 to 181 kg), mild to moderate renal impairment (CLcr 30 to < 90 mL/min based on the Cockcroft-Gault formula), or mild to severe hepatic impairment (Child-Pugh Class A, B, and C). The effect of severe renal impairment (CLcr < 30 mL/min) on the pharmacokinetics of alpelisib is unknown.

Drug Interaction Studies

Clinical Studies and Model-Informed Approaches

Acid Reducing Agents: No clinically significant differences in the pharmacokinetics of alpelisib were observed when used concomitantly with ranitidine (H2 receptor antagonist) and administered with food as directed.

Concomitant use of ranitidine decreased alpelisib AUC approximately 30% and Cmax by 51% with a single 300 mg oral dose (1.2 times the highest approved recommended dosage) of alpelisib under the fasted state. In the presence of a low-fat low-calorie meal, AUC was decreased by 21% and Cmax by 36% with ranitidine.

CYP3A4, CYP2C8, CYP2C9, CYP2C19 and CYP2B6 Substrates: Coadministration of repeated doses of alpelisib 300 mg with a single-dose of sensitive substrates of CYP3A4 (midazolam), CYP2C8 (repaglinide), CYP2C9 (warfarin), CYP2C19 (omeprazole) and CYP2B6 (bupropion), administered as a cocktail did not show clinically significant pharmacokinetic interactions.

No clinically significant differences in pharmacokinetics of everolimus (a substrate of CYP3A4 and P-gp) were observed when used concurrently with alpelisib.

Effect of CYP3A4 Inducers on Alpelisib: Coadministration of repeat doses of rifampin (a strong CYP3A4 inducer) with a single 300 mg dose of alpelisib decreased alpelisib Cmax by 38% and AUC by 57%, respectively. Coadministration of rifampin with repeat doses of 300 mg alpelisib decreased alpelisib Cmax by 59% and AUC by 74%, respectively.

Model-Informed Approaches

Coadministration of repeat doses of ketoconazole (a strong CYP3A4 inhibitor) with a single 300 mg dose of alpelisib is expected to increase alpelisib AUC by 37% or less.

Coadministration of repeat doses of efavirenz (a moderate CYP3A4 inducer) with a single 300 mg dose of alpelisib is expected to decrease alpelisib AUC by 30% or less.

In Vitro Studies

Effect of Transporter on Alpelisib: Alpelisib is a substrate of BCRP.

Effect of Alpelisib on Transporters: Alpelisib is an inhibitor of P-gp. Alpelisib has a low potential to inhibit BCRP, MRP2, BSEP, OATP1B1, OATP1B3, OCT1, OAT1, OAT3, OCT2, MATE1, and MATE2K at clinically relevant concentrations.

13 NONCLINICAL TOXICOLOGY

13.1 Carcinogenesis, Mutagenesis, Impairment of Fertility

Alpelisib was not carcinogenic in a 2-year carcinogenicity study conducted in rats when administered by daily oral gavage at doses up to 4 mg/kg (approximately 0.5 to 0.2 times the initial recommended doses of 50 mg and 250 mg in pediatric and adult patients, respectively, based on BSA).

Alpelisib was not mutagenic in an in vitro bacterial reverse mutation (Ames) assay, or aneugenic or clastogenic in human cell micronucleus and chromosome aberration tests. Alpelisib was not genotoxic in an in vivo rat micronucleus test.

In a fertility and early embryonic development study in rats, female animals were administered alpelisib doses of 3, 10, and 20 mg/kg/day orally. Animals were dosed for 4-weeks prior to pairing, during the mating period, and up to Gestation Day 6. At the dose of 20 mg/kg/day, alpelisib increased pre- and post-implantation losses, leading to reduced numbers of implantation sites and live embryos. These findings were observed at doses approximately 2.4 to 0.8 times the initial recommended doses of 50 mg and 250 mg in pediatric and adult patients, respectively, based on body surface areas (BSA). In a repeated-dose toxicity study in rats, adverse effects in female reproductive organs included vaginal atrophy and estrous cycle variations in rats at doses ≥ 6 mg/kg/day (approximately 0.7 to 0.2 times the initial recommended doses of 50 mg and 250 mg in pediatric and adult patients, respectively, based on BSA).

In a male fertility study, alpelisib administered orally at doses of 3, 10 and 20 mg/kg/day for up to 99 days (10-weeks prior to pairing, during mating period and continuing during post-pairing) to male rats, resulted in reduced weights of seminal vesicles and prostate, which correlated with atrophy and/or reduced secretion in prostate and seminal vesicles at ≥ 10 mg/kg/day (approximately 1.2 to 0.4 times the initial recommended doses of 50 mg and 250 mg in pediatric and adult patients, respectively, based on BSA). No adverse effects on male fertility parameters were observed at doses up to 20 mg/kg/day.

14 CLINICAL STUDIES

The efficacy of VIJOICE was assessed in EPIK-P1 (NCT04285723), a single-arm clinical study in patients who were treated as part of an expanded access program for compassionate use which enrolled patients across seven sites in five countries (France, Spain, US, Ireland, and Australia). Eligible patients 2 years of age and older with PIK3CA-Related Overgrowth Spectrum (PROS) who received VIJOICE had clinical manifestations of PROS that were assessed by the treating physician as severe or life-threatening and necessitating systemic treatment and had documented evidence of mutation in the PIK3CA gene. Patients received VIJOICE at dosages based on age ranging from 50 mg to 250 mg orally once daily.

The efficacy of VIJOICE was evaluated in a total of 37 patients with at least one target lesion identified on imaging performed within 24 weeks prior to receipt of the first dose of VIJOICE. The median age of patients was 14 years (range: 2 to 38); 22% of patients were 2 to 5 years, 22% were 6 to 11 years, 27% were 12 to less than 18 years of age, and 30% were ≥ 18 years; 57% were female, 11% were White and race was not reported for 89%. Ninety-two percent of patients had congenital overgrowth and 8% had early childhood-onset. Patients had heterogeneous manifestations of PROS, including CLOVES (81%), Megalencephaly-Capillary Malformation Polymicrogyria (MCAP; 8%), Klippel-Trenaunay Syndrome (KTS; 2.7%), Facial Infiltrating Lipomatosis (FIL; 8%), and Other (5%). Five percent (5%) of patients had concurrent manifestations of CLOVES and MCAP.

The major efficacy outcome measure for the study was the proportion of patients with radiological response at Week 24 as determined by blinded independent central review (BICR), defined as a ≥ 20% reduction from baseline in the sum of measurable target lesion volume (1 to 3 lesions) confirmed by at least one subsequent imaging assessment, in the absence of a ≥ 20% increase from baseline in any target lesion, progression of non-target lesions, or appearance of a new lesion. An additional efficacy outcome measure was duration of response, defined as the time from the first documented response to the date of the first documented disease progression or death due to any cause.

Efficacy results are presented in Table 12.

Table 12: Efficacy Results at Week 24 in EPIK-P1
Efficacy parameters | All patients N = 37
Response ratea,b
Responders, n (%) 95% CI | 10 (27) (14, 44)
Duration of response (DOR)
Median in months (range) | NR (0.9+, 42.9+)
% ≥ 6 months | 70
% ≥ 12 months | 60
Abbreviation: +, censored observation.
aConfirmed response as determined by blinded independent central review (BICR).
bPatients without any response assessment at Week 24 were considered non-responders.

16 HOW SUPPLIED/STORAGE AND HANDLING

VIJOICE (alpelisib) 50 mg, 125 mg, and 200 mg film-coated tablets are available in blister packs based on daily dose as described in Table 13.

Table 13: VIJOICE Tablets Daily Dose Blister Packs
Daily dose | Each carton contains | Each child-resistant blister pack contains | Appearance of tablet | NDC
50 mg daily dose | One 28-day supply blister pack | 28 tablets: 50 mg alpelisib per tablet | Light yellow, unscored, round and curved with beveled edges, debossed with “C7” on one side and “NVR” on the other side | NDC 0078-1021-84
125 mg daily dose | One 28-day supply blister pack | 28 tablets: 125 mg alpelisib per tablet | Dark yellow, unscored, ovaloid and curved with beveled edges, debossed with “Y7” on one side and “NVR” on the other side | NDC 0078-1028-84
250 mg daily dose | Two 14-day supply blister packs (56 tablets total) | 14 tablets: 200 mg alpelisib per tablet, and 14 tablets: 50 mg alpelisib per tablet | Pale yellow, unscored, ovaloid and curved with beveled edges, debossed with “CL7” on one side and “NVR” on the other side Light yellow, unscored, round and curved with beveled edges, debossed with “C7” on one side and “NVR” on the other side | NDC 0078-1035-02

Table 14: VIJOICE Oral Granules
Daily dose | Each carton contains | Each child-resistant packet contains | Appearance | NDC
50 mg daily dose | 28 packets (28-day supply of single-use packets) | 50 mg alpelisib | White to almost white free flowing mixture of powder and granules | NDC 0078-1175-51

Store at 20°C to 25°C (68°F to 77°F), excursions permitted between 15°C and 30°C (59°F and 86°F) [see USP Controlled Room Temperature].

17 PATIENT COUNSELING INFORMATION

Advise the patient and their caregivers to read the FDA-approved patient labeling (Patient Information).

Severe Hypersensitivity

Inform patients and their caregivers of the signs and symptoms of hypersensitivity. Advise patients and their caregivers to contact their healthcare provider immediately for signs and symptoms of hypersensitivity [see Warnings and Precautions (5.1)].

Severe Cutaneous Adverse Reactions

Inform patients and their caregivers of the signs and symptoms of severe cutaneous adverse reactions (SCARs). Advise patients and their caregivers to contact their healthcare provider immediately for signs and symptoms of SCARs (e.g., a prodrome of fever, flu-like symptoms, mucosal lesions, progressive skin rash, or lymphadenopathy) [see Warnings and Precautions (5.2)].

Hyperglycemia

Advise patients and their caregivers that VIJOICE may cause hyperglycemia and the need to monitor fasting glucose periodically during therapy. Advise patients and their caregivers of the signs and symptoms of hyperglycemia (e.g., excessive thirst, urinating more often than usual or higher amount of urine than usual, or increased appetite with weight loss) [see Warnings and Precautions (5.3)].

Pneumonitis

Inform patients and their caregivers that VIJOICE may cause pneumonitis and to immediately report new or worsening respiratory symptoms [see Warnings and Precautions (5.4)].

Diarrhea or Colitis

Advise patients and their caregivers that VIJOICE may cause diarrhea, which may be severe, and to start anti-diarrheal treatment, increase oral fluids, and notify their healthcare provider if diarrhea occurs while taking VIJOICE [see Warnings and Precautions (5.5)].

Advise patients and their caregivers that VIJOICE may cause colitis and to notify their healthcare provider immediately of any symptoms of colitis, such as abdominal pain and mucus or blood in stool, while taking VIJOICE [see Warnings and Precautions (5.5)].

Alopecia

Advise patients and caregivers that VIJOICE may cause alopecia [see Adverse Reactions (6.1)]. Advise patients and caregivers to contact a dermatologist if alopecia becomes a concern [see Dosage and Administration (2.5)].

Embryo-Fetal Toxicity

- Inform pregnant women and females of reproductive potential of the potential risk to a fetus. Advise females to inform their healthcare provider of a known or suspected pregnancy [see Warnings and Precautions (5.6) and Use in Specific Populations (8.1)].
- Advise females of reproductive potential to use effective contraception during treatment with VIJOICE and for 1 week after the last dose [see Use in Specific Populations (8.3)].
- Advise male patients with female partners of reproductive potential to use condoms and effective contraception during treatment with VIJOICE and for 1 week after the last dose [see Use in Specific Populations (8.3)].

Lactation

Advise women not to breastfeed during treatment with VIJOICE and for 1 week after the last dose [see Use in Specific Populations (8.2)].

Infertility

Advise males and females of reproductive potential that VIJOICE may impair fertility [see Use in Specific Populations (8.3)].

Drug Interactions

Advise patients and their caregivers to inform their healthcare providers of all concomitant medications, herbal and dietary supplements [see Drug Interactions (7.1)].

Dosing

Instruct patients and their caregivers of the following:

- Take VIJOICE with food at approximately the same time each day [see Dosage and Administration (2.3)].
- Swallow the tablets whole (tablets should not be crushed, chewed, or split prior to swallowing) [see Dosage and Administration (2.4)].
- For patients unable to swallow tablets, advise how to prepare an oral suspension using the tablets or how to take the oral granules (if applicable) [see Dosage and Administration (2.4)].
- If a dose of VIJOICE is missed, it can be taken with food within 9 hours after the time it is usually taken. After more than 9 hours, skip the dose for that day. The next day, take VIJOICE at the usual time. Instruct patients not to take 2 doses to make up for a missed dose [see Dosage and Administration (2.3)].
- If vomiting occurs after taking the dose of VIJOICE, they should not take an additional dose on that day and should resume the usual dosing schedule the next day at the usual time [see Dosage and Administration (2.3)].

Distributed by
Novartis Pharmaceuticals Corporation
East Hanover, New Jersey 07936

© Novartis

T2025-38

PATIENT INFORMATION

VIJOICE® (vi’ joiz)
(alpelisib)
tablets

VIJOICE® (vi’ joiz)
(alpelisib)
oral granules

What is VIJOICE?
VIJOICE is a prescription medicine used to treat adults and children 2 years of age and older with severe phosphatidylinositol-3-kinase catalytic subunit alpha (PIK3CA)-Related Overgrowth Spectrum (PROS).
It is not known if VIJOICE is safe and effective in children below 2 years of age.

Do not take VIJOICE if you have had a severe allergic reaction to alpelisib or are allergic to any of the ingredients in VIJOICE.

- See the end of this Patient Information leaflet for a complete list of the ingredients in VIJOICE.
- See “What are the possible side effects of VIJOICE?” for signs and symptoms of severe allergic reactions.

Before you take VIJOICE, tell your healthcare provider about all of your medical conditions, including if you:

- have a history of diabetes.
- have a history of skin rash, redness of skin, blistering of the lips, eyes or mouth, or skin peeling.
- are pregnant or plan to become pregnant. VIJOICE can harm your unborn baby.
  Females who are able to become pregnant:
  - Your healthcare provider will check to see if you are pregnant before you start treatment with VIJOICE.
  - You should use effective birth control (contraception) during treatment with VIJOICE and for 1 week after the last dose. Talk to your healthcare provider about birth control methods that may be right for you during this time.
  - If you become pregnant or think you are pregnant, tell your healthcare provider right away.
  Males with female partners who are able to become pregnant should use condoms and effective birth control during treatment with VIJOICE and for 1 week after the last dose. If your female partner becomes pregnant, tell your healthcare provider right away.
- are breastfeeding or plan to breastfeed. It is not known if VIJOICE passes into your breast milk. Do not breastfeed during treatment with VIJOICE and for 1 week after the last dose.

Tell your healthcare provider about all of the medicines you take, including prescription and over-the-counter medicines, vitamins, and herbal supplements. VIJOICE and other medicines may affect each other causing side effects. Know the medicines you take. Keep a list of them to show your healthcare provider or pharmacist when you get a new medicine.

How should I take VIJOICE?

- Read the detailed “Instructions for Use” that comes with VIJOICE for information about the right way to prepare and take or give a dose of VIJOICE tablets or oral granules.
- Take VIJOICE exactly as your healthcare provider tells you.
- Do not change your dose or stop taking VIJOICE unless your healthcare provider tells you.
- Take VIJOICE 1 time each day, at about the same time each day.
- Take VIJOICE with food.
- VIJOICE comes as tablets and oral granules. Your healthcare provider will prescribe the dosage form that is right for you:
  - If your prescribed daily dose is 50 mg, your healthcare provider may prescribe VIJOICE tablets or VIJOICE oral granules.
  - If your prescribed daily dose is 125 mg or 250 mg, you can only take VIJOICE tablets.
- Do not use multiple packets of 50 mg oral granules or part of a packet to prepare a dose. Do not combine VIJOICE tablets with VIJOICE oral granules to prepare your prescribed dose.
- If you miss a dose of VIJOICE, you may take it with food up to 9 hours after the time you usually take it. If it has been more than 9 hours after you usually take your dose, skip the dose for that day. The next day, take the dose at your usual time. Do not take 2 doses to make up for a missed dose.
- If you vomit after taking a dose of VIJOICE, do not take another dose on that day. Take your next dose at your usual time.
- If you take too much VIJOICE, call your healthcare provider or go to the nearest hospital emergency room right away.

VIJOICE tablets:

- VIJOICE tablets can be swallowed whole, or prepared as a suspension to take or give by mouth or through a feeding tube.
- If you are taking or giving VIJOICE tablets whole:
  - Swallow VIJOICE tablets whole and take with food. Do not chew, divide, or crush the tablets.
  - Do not take VIJOICE tablets that are broken, cracked, or that look damaged.
- If you cannot swallow tablets whole or need to use a feeding tube, you will need to mix VIJOICE tablets with water before taking or giving the dose.

VIJOICE oral granules:

- VIJOICE oral granules can be placed directly onto the tongue and swallowed with water, or mixed with a beverage or soft food to take or give by mouth, or mixed with water to give through a feeding tube.

What are the possible side effects of VIJOICE?
VIJOICE may cause serious side effects, including:

- Severe allergic reactions. Tell your healthcare provider or get medical help right away if you have trouble breathing, swelling of the face or throat, flushing, rash, fever, or fast heart rate during treatment with VIJOICE.
- Severe skin reactions. Tell your healthcare provider or get medical help right away if you get severe rash or rash that keeps getting worse, reddened skin, flu-like symptoms, blistering of the lips, eyes or mouth, blisters on the skin or skin peeling, with or without fever.
- High blood sugar levels (hyperglycemia). Hyperglycemia is common with VIJOICE and may be severe. Your healthcare provider will monitor your sugar levels before you start and during treatment with VIJOICE. Your healthcare provider may monitor your sugar levels more often if you have a history of diabetes. Tell your healthcare provider right away if you develop symptoms of hyperglycemia, including:

◦ excessive thirst
◦ dry mouth
◦ more frequent urination than usual or a higher amount of urine than normal
◦ increased appetite with weight loss

◦ confusion
◦ nausea
◦ vomiting
◦ fruity odor on breath
◦ difficulty breathing
◦ dry or flushed skin

- Lung problems (pneumonitis). Tell your healthcare provider right away if you develop new or worsening symptoms of lung problems, including:

◦ shortness of breath or trouble breathing
◦ cough

◦ chest pain

- Diarrhea or colitis (inflammation of your intestines). Diarrhea is common with VIJOICE and may be severe. Severe diarrhea can lead to the loss of too much body water (dehydration) and kidney injury. Tell your healthcare provider right away if you develop diarrhea, stomach-area (abdominal) pain, or see mucus or blood in your stool during treatment with VIJOICE. Your healthcare provider may tell you to drink more fluids or take medicines to treat diarrhea or colitis.

Your healthcare provider may tell you to decrease your dose, temporarily stop your treatment, or completely stop your treatment with VIJOICE if you get certain serious side effects.
The most common side effects of VIJOICE include:

• diarrhea

• mouth sores (stomatitis)

• high blood sugar

VIJOICE may cause hair loss (alopecia). Talk to a skin specialist (dermatologist) if this is a concern for you.
VIJOICE may affect fertility in males and in females who are able to become pregnant. Talk to your healthcare provider if this is a concern for you.
These are not all of the possible side effects of VIJOICE.
Call your doctor for medical advice about side effects. You may report side effects to FDA at 1-800-FDA-1088.

How should I store VIJOICE?

- Store VIJOICE at room temperature between 68°F to 77°F (20°C to 25°C).

Keep VIJOICE and all medicines out of the reach of children.

General information about the safe and effective use of VIJOICE.
Medicines are sometimes prescribed for purposes other than those listed in a Patient Information leaflet. Do not use VIJOICE for a condition for which it was not prescribed. Do not give VIJOICE to other people, even if they have the same symptoms you have. It may harm them. You can ask your healthcare provider or pharmacist for more information about VIJOICE that is written for health professionals.

What are the ingredients in VIJOICE?
Active ingredient: alpelisib
Inactive ingredients for VIJOICE tablets: hypromellose, magnesium stearate, mannitol, microcrystalline cellulose, and sodium starch glycolate. The film-coating contains hypromellose, iron oxide red (applicable only to 50 mg and 200 mg strengths), iron oxide yellow, macrogol/polyethylene glycol (PEG) 4000, talc, and titanium dioxide.
Inactive ingredients for VIJOICE oral granules: hypromellose, magnesium stearate, mannitol, microcrystalline cellulose, and sodium starch glycolate.
Distributed by: Novartis Pharmaceuticals Corporation, East Hanover, New Jersey 07936
© Novartis
For more information, go to www.VIJOICE.com or call 1-888-VIJOICE (1-888-845-6423).

This Patient Information has been approved by the U.S. Food and Drug Administration.

Revised: 7/2025

T2025-39

INSTRUCTIONS FOR USE
VIJOICE® [vi’ joiz]
(alpelisib)
tablets

This Instructions for Use contains information on how to prepare and take or give a dose of VIJOICE tablets.

Read this Instructions for Use carefully before taking or giving VIJOICE tablets.

Talk to your healthcare provider or pharmacist if you have any questions. You can also call Novartis Pharmaceuticals Corporation at 1-888-845-6423 for more information.

Important Information You Need to Know Before Taking or Giving VIJOICE

- Take or give VIJOICE exactly as your healthcare provider tells you.
- Do not change your dose or stop taking VIJOICE unless your healthcare provider tells you.
- Take VIJOICE 1 time each day, at about the same time each day.
- Take VIJOICE with food.
- Do not combine VIJOICE tablets with VIJOICE oral granules to prepare your prescribed dose.
- If you miss a dose of VIJOICE, you may take it with food up to 9 hours after the time you usually take it. If it has been more than 9 hours after you usually take your dose, skip the dose for that day. The next day, take the dose at your usual time. Do not take 2 doses to make up for a missed dose.
- If you vomit after taking a dose of VIJOICE, do not take another dose on that day. Take your next dose at your usual time.
- If you take too much VIJOICE, call your healthcare provider or go to the nearest hospital emergency room right away.

Storing VIJOICE tablets

- Store VIJOICE tablets at room temperature between 68°F to 77°F (20°C to 25°C).
- Keep VIJOICE and all medicines out of the reach of children.

Preparing and taking or giving VIJOICE tablets
You can take or give VIJOICE tablets whole by mouth, or mixed with water (suspension) by mouth or through a feeding tube as described in the sections below:
Taking or giving VIJOICE tablets whole by mouth
Swallow VIJOICE tablets whole and take with food.

- Do not chew, divide, or crush the tablets.
- Do not take VIJOICE tablets that are broken, cracked, or that look damaged.

Taking or giving VIJOICE tablets mixed with water (suspension) by mouth
If you cannot swallow tablets whole, VIJOICE tablets can be prepared as a suspension and taken or given by mouth.
Gather the following supplies (see Figure A):

- the number of VIJOICE tablet(s) needed for your prescribed dose
- water
- a clean empty cup
- a spoon

Step 1. Wash and dry your hands.
Step 2. Place VIJOICE tablets into a cup that contains 2 to 4 ounces of water. Use water only.
Step 3. Let the tablets stand in water for about 5 minutes.
Step 4. Crush the tablets with a spoon and stir to disperse the tablets in water (suspension). The suspension will be cloudy and you may see tablet particles (see Figure B).
Step 5. Drink all of the suspension right away. If you cannot take or give it right away, take or give the suspension within 60 minutes of preparing the dose. Stir the suspension again with the same spoon before drinking it.
Step 6. Add about 1 to 2 ounces of water to the same cup and stir with the same spoon. Then drink all of the suspension to make sure the entire dose is taken.
Step 7. Repeat Step 6 until there are no tablet particles remaining in the cup.
Step 8. Wash your hands and all supplies used to take or give VIJOICE tablets.
Throw away any VIJOICE suspension that is not taken within 60 minutes after it is prepared.

Figure A
Figure B

Giving VIJOICE tablets mixed with water (suspension) through a feeding tube
VIJOICE tablets may be given through a feeding tube, according to the manufacturer’s instructions and as directed by your healthcare provider. Only use silicone or polyurethane nasogastric tubes with a French size 5 to 12, or silicone gastric tubes with a French size 12 to 24.
Gather the following supplies (see Figure C):

- the number of VIJOICE tablet(s) needed for your prescribed dose
- water
- a clean empty cup
- a spoon
- an enteral syringe

Figure C

Step 1. Wash and dry your hands.
Step 2. Place VIJOICE tablets into a cup that contains 1 to 2 ounces (about 30 to 60 mL) of water. Use water only.
Step 3. Let the tablets stand in water for about 5 minutes.
Step 4. Crush the tablets with a spoon and stir to disperse the tablets in water (suspension). The suspension will be cloudy and you may see tablet particles (see Figure B).
Step 5. Draw up all of the suspension from the cup into an enteral syringe (see Figure D) and give it through the feeding tube right away. If you cannot give it right away, give the suspension within 60 minutes of preparing the dose. Stir the suspension again with the same spoon before drawing it up.
Step 6. Add about 1 to 2 ounces (about 30 to 60 mL) of water to the same cup and stir with the same spoon.
Step 7. Draw up all of the suspension into the same enteral syringe and give it through the feeding tube.
Step 8. Repeat Steps 6 and 7 if there are tablet particles remaining in the enteral syringe or in the cup.
Step 9. Wash your hands and all supplies used to give VIJOICE tablets. Follow the manufacturer’s instructions to clean your enteral syringe.
Throw away any VIJOICE suspension that is not taken within 60 minutes after it is prepared.

Figure D

Distributed by:
Novartis Pharmaceuticals Corporation East Hanover, New Jersey 07936
© Novartis

This Instructions for Use has been approved by the U.S. Food and Drug Administration.

Issued: 7/2025

T2025-40

INSTRUCTIONS FOR USE
VIJOICE® [vi’ joiz]
(alpelisib)
oral granules

This Instructions for Use contains information on how to prepare and take or give a dose of VIJOICE oral granules.

Read this Instructions for Use carefully before taking or giving VIJOICE oral granules.

Talk to your healthcare provider or pharmacist if you have any questions. You can also call Novartis Pharmaceuticals Corporation at 1-888-845-6423 for more information.

Important Information You Need to Know Before Taking or Giving VIJOICE

- Take or give VIJOICE exactly as your healthcare provider tells you.
- Do not change your dose or stop taking VIJOICE unless your healthcare provider tells you.
- Take VIJOICE 1 time each day, at about the same time each day.
- Take VIJOICE with food.
- Each VIJOICE oral granules packet is for single use only.
- Do not use the packet if the packet seal is broken.
- Do not use multiple packets of 50 mg oral granules or part of a packet to prepare a dose.
- Do not combine VIJOICE tablets with VIJOICE oral granules to prepare your prescribed dose.
- If you miss a dose of VIJOICE, you may take it with food up to 9 hours after the time you usually take it. If it has been more than 9 hours after you usually take your dose, skip the dose for that day. The next day, take the dose at your usual time. Do not take 2 doses to make up for a missed dose.
- If you vomit after taking a dose of VIJOICE, do not take another dose on that day. Take your next dose at your usual time.
- If you take too much VIJOICE, call your healthcare provider or go to the nearest hospital emergency room right away.

Storing VIJOICE oral granules

- Store VIJOICE oral granules at room temperature between 68°F to 77°F (20°C to 25°C).
- Keep VIJOICE and all medicines out of the reach of children.

Preparing and taking or giving VIJOICE oral granules

You can take or give VIJOICE oral granules directly onto the tongue swallowed with water, or mixed with a beverage or soft food by mouth, or mixed with water through a feeding tube as described in the sections below:

Taking or giving VIJOICE oral granules directly onto the tongue
Gather the following supplies (see Figure A):

- 1 VIJOICE oral granules packet
- scissors
- water

Step 1. Wash and dry your hands.
Step 2. Hold the packet of oral granules with the cut line on top.
Step 3. Shake the packet gently to ensure the VIJOICE oral granules are in the lower part of the packet.
Step 4. Using scissors, open the packet along the cut line.
Step 5. Pour all the oral granules from 1 VIJOICE oral granules packet directly onto the tongue by tapping the side and top of the packet, and swallow it with about 2 to 4 ounces of water (see Figure B).
Step 6. If there is any medicine remaining in the mouth, rinse the mouth with additional water and swallow to make sure the entire dose is taken.
Step 7. Wash your hands and all supplies used to take or give VIJOICE oral granules.

Figure AFigure B

Taking or giving VIJOICE oral granules mixed with a beverage or soft food by mouth
Gather the following supplies (see Figure C):

- 1 VIJOICE oral granules packet
- scissors
- the beverage or soft food of your choice among water, milk, apple juice, applesauce or yogurt. See Step 6.
- a clean empty cup
- a spoon

Figure C

Step 1. Wash and dry your hands.
Step 2. Hold the packet of oral granules with the cut line on top.
Step 3. Shake the packet gently to ensure the VIJOICE oral granules are in the lower part of the packet.
Step 4. Using scissors, open the packet along the cut line.
Step 5. Pour the oral granules from 1 VIJOICE oral granules packet into a cup by tapping the side and top of the packet (see Figure D).
Step 6. Add 1 to 3 teaspoons of a beverage (water, milk, or apple juice) or soft food (applesauce or yogurt), stir with a spoon and take or give the mixture right away. If you do not take or give it right away, take or give the mixture within 60 minutes of preparing the dose. Stir the mixture with the same spoon before taking or giving it.
Step 7. Rinse the cup with up to 2 ounces of water, milk, or apple juice. Drink the rinse right away to make sure the entire dose is taken. Repeat this step until there are no oral granules remaining in the cup.
Step 8. Wash your hands and all supplies used to take or give VIJOICE oral granules.
Throw away any VIJOICE oral granules mixture that is not taken within 60 minutes after it is prepared.

Figure D

Giving VIJOICE oral granules mixed with water (suspension) through a feeding tube
VIJOICE oral granules may be given through a feeding tube, according to the manufacturer’s instructions and as directed by your healthcare provider. Only use silicone or polyurethane nasogastric tubes with a French size 8 to 12, or silicone gastric tubes with a French size 12 to 24.
Gather the following supplies (see Figure E):

- 1 VIJOICE oral granules packet
- water
- a clean empty cup
- a spoon
- an enteral syringe

Figure E

Step 1. Wash and dry your hands.
Step 2. Pour the oral granules from 1 VIJOICE oral granules packet into a cup by tapping the side and top of the packet (see Figure D).
Step 3. Add 4 teaspoons (about 20 mL) of water to the same cup and stir gently with a spoon to disperse the oral granules in the water (suspension). Use water only.
Step 4. Draw up all of the suspension from the cup into an enteral syringe (see Figure F) and give it through the feeding tube right away. If you cannot give it right away, give the suspension within 60 minutes of preparing the dose. Stir the suspension again with the same spoon before drawing it up.
Step 5. Add 4 teaspoons (about 20 mL) of water to the same cup and stir with the same spoon.
Step 6. Draw up all of the suspension from the cup into the same enteral syringe and give it through the feeding tube.
Step 7. Repeat Steps 5 and 6 until there are no oral granules remaining in the cup or in the syringe.
Step 8. Wash your hands and all supplies used give VIJOICE oral granules. Follow the manufacturer’s instructions to clean your enteral syringe.
Throw away any VIJOICE suspension that is not taken within 60 minutes after it is prepared.

Figure F

Distributed by: Novartis Pharmaceuticals Corporation East Hanover, New Jersey 07936
© Novartis

This Instructions for Use has been approved by the U.S. Food and Drug Administration.

Issued: 7/2025

T2025-41

PRINCIPAL DISPLAY PANEL

Vijoice®
(alpelisib) tablets

NDC 0078-1021-84

50 mg daily dose

Take one 50 mg tablet once daily

Rx only

Recommended Dosage: Take one 50 mg tablet once daily with food.
Swallow tablets whole. DO NOT chew, crush, or split tablets.

Directions: See enclosed Instructions for Use for administration
instructions, including options for patients who are unable to swallow
whole tablets.

28-Day Supply

Contains: One blister pack containing 28 tablets

NOVARTIS

PRINCIPAL DISPLAY PANEL

Vijoice®
(alpelisib) tablets

NDC 0078-1028-84

125 mg daily dose

Take one 125 mg tablet once daily

Rx only

Recommended Dosage: Take one 125 mg tablet once daily with food.
Swallow tablets whole. DO NOT chew, crush, or split tablets.

Directions: See enclosed Instructions for Use for administration
instructions, including options for patients who are unable to swallow
whole tablets.

28-Day Supply

Contains: One blister pack containing 28 tablets

NOVARTIS

PRINCIPAL DISPLAY PANEL

Vijoice®
(alpelisib) tablets

NDC 0078-1035-02

250 mg daily dose

Take one 200 mg tablet and one 50 mg tablet once daily

Rx only

Recommended Dosage: Take one 200 mg tablet and one 50 mg
tablet once daily with food. Swallow tablets whole. DO NOT chew,
crush, or split tablets.

Directions: See enclosed Instructions for Use for administration
instructions, including options for patients who are unable to
swallow whole tablets.

28-Day Supply (56 Tablets)

Contains: Two 14-day blister packs each containing 28 tablets:

200 mg
14 tablets per pack

50 mg
14 tablets per pack

NOVARTIS

PRINCIPAL DISPLAY PANEL

Rx only

NDC 0078-1175-51

Vijoice®
(alpelisib) oral granules

50 mg daily dose

Take one 50 mg packet once daily

Directions: See enclosed Instructions For
Use for administration instructions.

28 Packets

NOVARTIS